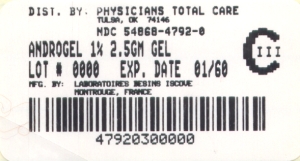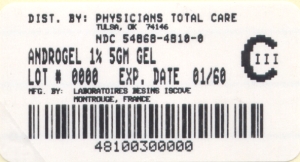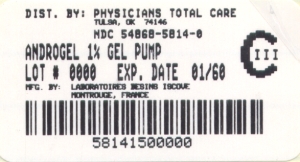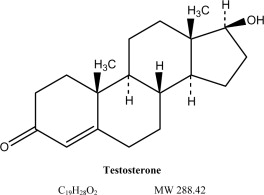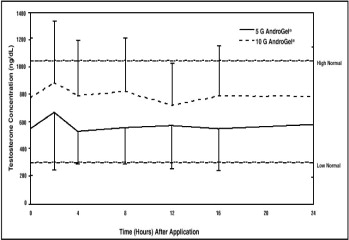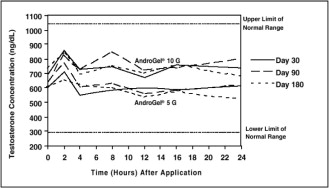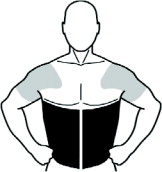 DRUG LABEL: Androgel
NDC: 54868-5814 | Form: GEL
Manufacturer: Physicians Total Care, Inc.
Category: prescription | Type: HUMAN PRESCRIPTION DRUG LABEL
Date: 20111215
DEA Schedule: CIII

ACTIVE INGREDIENTS: testosterone 10 mg/1 g
INACTIVE INGREDIENTS: carbomer homopolymer type C; alcohol; isopropyl myristate; water; sodium hydroxide

HIGHLIGHTS OF PRESCRIBING INFORMATION

These highlights do not include all the information needed to use AndroGel safely and effectively. See full prescribing information for AndroGel.
AndroGel® (testosterone gel) 1% for topical use CIII
Initial U.S. Approval: 1953

WARNING: SECONDARY EXPOSURE TO TESTOSTERONE

- Virilization has been reported in children who were secondarily exposed to testosterone gel (5.2, 6.2).
- Children should avoid contact with unwashed or unclothed application sites in men using testosterone gel (5.2).
- Healthcare providers should advise patients to strictly adhere to recommended instructions for use (5.2).

RECENT MAJOR CHANGES

- Boxed Warning 9/2009
- WARNINGS AND PRECAUTIONS (5.2) 9/2009

1 INDICATIONS AND USAGE

AndroGel is an androgen indicated for replacement therapy in males for conditions associated with a deficiency or absence of endogenous testosterone:

- Primary Hypogonadism (Congenital or Acquired) (1.1)
- Hypogonadotropic Hypogonadism (Congenital or Acquired) (1.1)

2 DOSAGE AND ADMINISTRATION

- Recommended starting dose: 5 g for adult males, applied topically once daily (2.1).
- Apply to clean, dry, intact skin of shoulders and upper arms and/or abdomen. Do NOT apply AndroGel to the genitals (2.1).
- Dose adjustment for adult males: If serum testosterone level is below the normal range, adjust dose from 5 g to 7.5 g and from 7.5 g to 10 g (2.3).

3 DOSAGE FORMS AND STRENGTHS

AndroGel (testosterone gel) 1% for topical use is available as:

- 2 x 75 g pumps (each pump dispenses 60 metered 1.25 g doses) (3)
- 2.5 g packet or 5 g packet (3)

4 CONTRAINDICATIONS

- Men with carcinoma of the breast or known or suspected prostate cancer (4, 5.1).
- Pregnant or breast feeding women. Testosterone may cause fetal harm (4).

5 WARNINGS AND PRECAUTIONS

- Patients with benign prostatic hyperplasia (BPH) treated with androgens are at an increased risk for worsening of signs and symptoms of BPH (5.1).
- Secondary exposure to testosterone in children and women can occur with use of testosterone gel (5.2). Cases of secondary exposure resulting in virilization of children have been reported (6.2).
  - Children and women should avoid contact with unwashed or unclothed application site(s) in men using testosterone gel.
  - To minimize the potential for transfer to others, patients using AndroGel should apply the product as directed and strictly adhere to the following (5.2):
    - Wash hands with soap and water after application.
    - Cover the application site with clothing after the gel has dried.
    - Wash the application site thoroughly with soap and water prior to any situation where skin-to-skin contact of the application site with another person is anticipated.
- Signs of virilization in children and women and the possibility of secondary exposure to testosterone gel should be brought to the attention of the healthcare provider. Testosterone gel should be promptly discontinued until the cause of the virilization is identified (5.2).
- Due to lack of controlled evaluations in women and potential virilizing effects, AndroGel is not indicated for use in women (5.3).
- Exogenous administration of androgens may lead to azoospermia (5.4).
- Edema may be a complication in patients with preexisting cardiac, renal, or hepatic disease (5.6, 6.2).
- Gynecomastia, enlargement of breast, may develop (5.7).
- Sleep apnea may occur in those with risk factors (5.8).
- Monitor serum testosterone, prostatic specific antigen, hemoglobin, hematocrit, liver function test, and lipid levels periodically (2.3, 5.1, 5.9).
- Alcohol-based gels are flammable until dry (5.10).

6 ADVERSE REACTIONS

Most common adverse reactions (incidence ≥ 5%) are acne, application site reaction, abnormal lab tests, and prostatic disorders (6).

Cases of testosterone secondary exposure resulting in virilization of children have been reported (6.2). Reported signs and symptoms have included enlargement of the penis or clitoris, premature development of pubic hair, increased erections and libido, aggressive behavior, and advanced bone age. In most cases with a reported outcome, these signs and symptoms were reported to have regressed with removal of the exposure to testosterone gel (5.2, 6.2). In a few cases, however, enlarged genitalia did not fully return to age-appropriate normal size and bone age remained modestly greater than chronological age.

To report SUSPECTED ADVERSE REACTIONS, contact Abbott Laboratories at 1-800-241-1643 or FDA at 1-800-FDA-1088 or www.fda.gov/medwatch.

7 DRUG INTERACTIONS

- Androgens may decrease blood glucose, and therefore insulin requirement in diabetic patients (7.1).
- Use of testosterone with ACTH or corticosteroids may result in increased fluid retention. Use with caution, particularly in patients with cardiac, renal, or hepatic disease (7.2).
- Changes in anticoagulant activity may be seen with androgens. More frequent monitoring of INR and prothrombin time is recommended (7.3).

8 USE IN SPECIFIC POPULATIONS

- Pregnancy: AndroGel may cause teratogenic effects. AndroGel should not be used in pregnant women (4, 8.1).
- Nursing mothers should not use AndroGel (4, 8.3).
- Safety and efficacy of AndroGel in males < 18 years old has not been established (8.4).
- There have not been sufficient numbers of geriatric patients involved in controlled clinical studies utilizing AndroGel to determine whether efficacy in those > 65 differs from younger subjects. Additionally, there is insufficient long-term safety data in geriatric patients to assess the potential risks of cardiovascular disease and prostate cancer (8.5).
- No formal studies were conducted involving patients with renal or hepatic insufficiencies (8.6).

FULL PRESCRIBING INFORMATION

WARNING: SECONDARY EXPOSURE TO TESTOSTERONE

- Virilization has been reported in children who were secondarily exposed to testosterone gel [see Warnings and Precautions (5.2) and Adverse Reactions (6.2)].
- Children should avoid contact with unwashed or unclothed application sites in men using testosterone gel [see Warnings and Precautions (5.2)].
- Healthcare providers should advise patients to strictly adhere to recommended instructions for use [see Warnings and Precautions (5.2) ].

1 INDICATIONS AND USAGE

1.1 Testosterone Replacement Therapy

AndroGel, an androgen, is indicated for replacement therapy in adult males for conditions associated with a deficiency or absence of endogenous testosterone:

- Primary Hypogonadism (Congenital or Acquired) - testicular failure due to cryptorchidism, bilateral torsion, orchitis, vanishing testis syndrome, orchiectomy, Klinefelter's syndrome, chemotherapy, or toxic damage from alcohol or heavy metals. These men usually have low serum testosterone levels and gonadotropins (FSH, LH) above the normal range.
- Hypogonadotropic Hypogonadism (Congenital or Acquired) - idiopathic gonadotropin or luteinizing hormone-releasing hormone (LHRH) deficiency or pituitary-hypothalamic injury from tumors, trauma, or radiation. These men have low testosterone serum levels but have gonadotropins in the normal or low range.

2 DOSAGE AND ADMINISTRATION

2.1 General Dosing

The recommended starting dose of AndroGel is 5 g once daily (preferably in the morning) to clean, dry, intact skin of the shoulders and upper arms and/or abdomen (area of application should be limited to the area that will be covered by the patient's short sleeve t-shirt). AndroGel must not be applied to the genitals. AndroGel is supplied as either a pump or in individual packets. After applying the gel, the application site should be allowed to dry for a few minutes prior to dressing. Avoid fire, flames or smoking until the gel has dried since alcohol based products, including AndroGel, are flammable. Hands should be washed with soap and water after AndroGel has been applied. [see Warnings and Precautions (5.2, 5.10)].

2.2 Administration

Multi-Dose Pump

Patients should be instructed to prime the pump before using it for the first time by fully depressing the pump mechanism (actuation) 3 times and discard this portion of the product to assure precise dose delivery. After the priming procedure, patients should completely depress the pump one time (actuation) for every 1.25 g (AndroGel Pump) of product required to achieve the daily prescribed dosage. The product may be delivered directly into the palm of the hand and then applied to the desired application sites, either one pump actuation at a time or upon completion of all pump actuations required for the daily dose. Alternatively, the product can be applied directly to the application sites. Application directly to the sites may prevent loss of product that may occur during transfer from the palm of the hand onto the application sites. Table 1 has specific dosing guidelines for adult males when the 75 g AndroGel Pump is used.

Table 1: Specific Dosing Guidelines for Using the Adult Multi-Dose Pump
Prescribed Daily Dose | Number of Pump Actuations in 75 g Pump
5 g | 4 (once daily)
7.5 g | 6 (once daily)
10 g | 8 (once daily)

Packets

The entire contents should be squeezed into the palm of the hand and immediately applied to the application sites. Alternately, patients may squeeze a portion of the gel from the packet into the palm of the hand and apply to application sites. Repeat until entire contents have been applied.

2.3 Dose Adjustment and Patient Assessments

- To ensure proper dosing, serum testosterone levels should be measured at intervals and replaced to serum testosterone levels in the normal range. If the serum testosterone concentration is below the normal range, the daily AndroGel dose may be increased from 5 g to 7.5 g and from 7.5 g to 10 g for adult males as instructed by the physician. If the serum testosterone concentration exceeds the normal range, the daily AndroGel dose may be decreased. If the serum testosterone concentration consistently exceeds the normal range at a daily dose of 5 g, AndroGel therapy should be discontinued.

The following is general advice for treating and monitoring adult patients on AndroGel. No specific recommendations can be made.

- Prescribers should be aware that testosterone is contraindicated in men with known or suspected prostate cancer. Therefore, evaluation for prostate cancer prior to initiation of AndroGel therapy is appropriate [see Contraindications (4)].
- Based on results from controlled studies, serum PSA may rise when taking AndroGel. Therefore, periodic assessment of serum PSA is recommended in patients taking AndroGel [see Adverse Reactions (6.1)].
- Based on results from controlled studies, worsening of BPH may occur in patients taking AndroGel [see Adverse Reactions (6.1)]. Therefore, periodic assessments for signs and symptoms of BPH are recommended in patients taking AndroGel.
- Hematocrit, serum lipid profile, and liver function test should be monitored in patients taking AndroGel [see Warnings and Precautions (5.9)].

3 DOSAGE FORMS AND STRENGTHS

AndroGel (testosterone gel) 1% for topical use is available in either unit-dose packets or multiple-dose pumps. The 75 g (60 metered-dose) pump delivers 1.25 g of product when the pump mechanism is fully depressed once.

AndroGel is available in the following three package containers:

- 2 x 75 g pumps (each pump dispenses 60 metered 1.25 g doses)
- 2.5 g packet
- 5 g packet

4 CONTRAINDICATIONS

AndroGel should not be used in any of the following patients:

- Men with carcinoma of the breast or known or suspected carcinoma of the prostate [see Warnings and Precautions (5.1), Adverse Reactions (6.1), and Nonclinical Toxicology (13.1)].
- Women who are or may become pregnant, or who are breastfeeding. AndroGel can cause fetal harm when administered to a pregnant woman. AndroGel may cause serious adverse reactions in nursing infants. Exposure of a female fetus or nursing infant to androgens may result in varying degrees of virilization. Pregnant women or those who may become pregnant need to be aware of the potential for transfer of testosterone from men treated with AndroGel [see Warnings and Precautions (5.2) and Use in Specific Populations (8.1, 8.3)].
- Men with known hypersensitivity to any of its ingredients, including alcohol and soy products.

5 WARNINGS AND PRECAUTIONS

5.1 Benign Prostatic Hyperplasia and Potential Risk of Prostate Cancer

- Patients with BPH treated with androgens are at an increased risk for worsening of signs and symptoms of BPH.
- Patients treated with androgens may be at increased risk for prostate cancer. Evaluation of the patient for prostate cancer prior to initiating and during treatment with androgens is appropriate.
- Increases in serum PSA from baseline values were seen in approximately 18% of individuals in an open label study of 162 hypogonadal men treated with AndroGel for up to 42 months. Most of these increases were seen within the first year of therapy [see Contraindications (4), Warnings and Precautions (5.9), Adverse Reactions (6.1), and Nonclinical Toxicology (13.1)].

5.2 Potential for Secondary Exposure to Testosterone

Secondary exposure to testosterone in children and women can occur with testosterone gel use in men [see Clinical Studies (14.3)]. Cases of secondary exposure resulting in virilization of children have been reported in postmarketing surveillance. Signs and symptoms have included enlargement of the penis or clitoris, development of pubic hair, increased erections and libido, aggressive behavior, and advanced bone age. In most cases, these signs and symptoms regressed with removal of the exposure to testosterone gel. In a few cases, however, enlarged genitalia did not fully return to age-appropriate normal size, and bone age remained modestly greater than chronological age. The risk of transfer was increased in some of these cases by not adhering to precautions for the appropriate use of testosterone gel.

Inappropriate changes in genital size or development of pubic hair or libido in children, or changes in body hair distribution, significant increase in acne, or other signs of virilization in adult women should be brought to the attention of a physician and the possibility of secondary exposure to testosterone gel should also be brought to the attention of a physician. Testosterone gel should be promptly discontinued until the cause of virilization has been identified.

Testosterone may cause fetal harm in a pregnant woman due to virilization of a female fetus [see Use in Specific Populations (8.1)].

Strict adherence to the following precautions is advised in order to minimize the potential for secondary exposure to testosterone from AndroGel-treated skin:

- Children and women should avoid contact with unwashed or unclothed application site(s) of men using testosterone gel.
- AndroGel should only be applied to the shoulders, upper arms, and/or abdomen (area of application should be limited to the area that will be covered by the patient's short sleeve t-shirt).
- Patients should wash their hands immediately with soap and water after applying AndroGel.
- Patients should cover the application site(s) with clothing (e.g., a shirt) after the gel has dried.
- Prior to any situation in which skin-to-skin contact with the application site is anticipated, patients should wash the application site(s) thoroughly with soap and water to remove any testosterone residue.
- In the event that unwashed or unclothed skin to which AndroGel has been applied comes in direct contact with the skin of another person, the general area of contact on the other person should be washed with soap and water as soon as possible. Studies show that residual testosterone is removed from the skin surface by washing with soap and water.

5.3 Use in Women

Due to lack of controlled evaluations in women and potential virilizing effects, AndroGel is not indicated for use in women [see Use in Specific Populations (8.1, 8.3)].

5.4 Potential for Adverse Effects on Spermatogenesis

At large doses of exogenous androgens, spermatogenesis may be suppressed through feedback inhibition of pituitary follicle-stimulating hormone (FSH) which could possibly lead to adverse effects on semen parameters including sperm count.

5.5 Hepatic Adverse Effects

Prolonged use of high doses of orally active 17-alpha-alkyl androgens (e.g., methyltestosterone) has been associated with serious hepatic adverse effects (peliosis hepatis, hepatic neoplasms, cholestatic hepatitis, and jaundice). Peliosis hepatis can be a life-threatening or fatal complication. Long-term therapy with intramuscular testosterone enanthate has produced multiple hepatic adenomas. AndroGel is not known to produce these adverse effects.

There are rare reports of hepatocellular carcinoma in patients receiving long-term oral therapy with androgens in high doses. Withdrawal of the drugs did not lead to regression of the tumors in all cases.

5.6 Edema

Drugs in the androgen class may promote retention of sodium and water. Edema with or without congestive heart failure may be a serious complication in patients with preexisting cardiac, renal, or hepatic disease [see Adverse Reactions (6.2)].

5.7 Gynecomastia

Gynecomastia may develop and may persist in patients being treated with androgens, including AndroGel, for hypogonadism.

5.8 Sleep Apnea

The treatment of hypogonadal men with testosterone products may potentiate sleep apnea in some patients, especially those with risk factors such as obesity or chronic lung diseases [see Adverse Reactions (6.2)].

5.9 Laboratory Tests

- Increases in hematocrit, reflective of increases in red blood cell mass, may require lowering or discontinuation of testosterone. Increase in red blood cell mass may increase the risk for a thromboembolic event.
- Changes in serum lipid profile may require dose adjustment or discontinuation of testosterone therapy.
- Androgens may decrease levels of thyroxin-binding globulin, resulting in decreased total T4 serum levels and increased resin uptake of T3 and T4. Free thyroid hormone levels remain unchanged, however, and there is no clinical evidence of thyroid dysfunction.
- Androgens should be used with caution in cancer patients at risk of hypercalcemia (and associated hypercalciuria). Regular monitoring of serum calcium concentrations is recommended in these patients.

5.10 Flammable Until Dry

- Alcohol Based Products including AndroGel are flammable; therefore avoid fire, flame or smoking until the gel has dried.

6 ADVERSE REACTIONS

6.1 Clinical Trial Experience

Because clinical trials are conducted under widely varying conditions, adverse reaction rates observed in the clinical trials of a drug cannot be directly compared to rates in the clinical trials of another drug and may not reflect the rates observed in practice.

Clinical Trials in Hypogonadal Men

Table 2 shows the incidence of all adverse events judged by the investigator to be at least possibly related to treatment with AndroGel and reported by >1% of patients in a 180 Day, Phase 3 study.

Table 2: Adverse Events Possibly, Probably or Definitely Related to Use of AndroGel in the 180-Day Controlled Clinical Trial
Adverse Event | Dose of AndroGel
Adverse Event | 5 g | 7.5 g | 10 g
 | N = 77 | N = 40 | N = 78
Acne | 1% | 3% | 8%
Alopecia | 1% | 0% | 1%
Application Site Reaction | 5% | 3% | 4%
Asthenia | 0% | 3% | 1%
Depression | 1% | 0% | 1%
Emotional Lability | 0% | 3% | 3%
Gynecomastia | 1% | 0% | 3%
Headache | 4% | 3% | 0%
Hypertension | 3% | 0% | 3%
Lab Test Abnormal* | 6% | 5% | 3%
Libido Decreased | 0% | 3% | 1%
Nervousness | 0% | 3% | 1%
Pain Breast | 1% | 3% | 1%
Prostate Disorder** | 3% | 3% | 5%
Testis Disorder*** | 3% | 0% | 0%
*Lab test abnormal occurred in nine patients with one or more of the following events reported: elevated hemoglobin or hematocrit, hyperlipidemia, elevated triglycerides, hypokalemia, decreased HDL, elevated glucose, elevated creatinine, elevated total bilirubin.
**Prostate disorders included five patients with enlarged prostate, one with BPH, and one with elevated PSA results.
***Testis disorders were reported in two patients: one with left varicocele and one with slight sensitivity of left testis.

Other less common adverse reactions, reported in fewer than 1% of patients included: amnesia, anxiety, discolored hair, dizziness, dry skin, hirsutism, hostility, impaired urination, paresthesia, penis disorder, peripheral edema, sweating, and vasodilation.

In this 180 day clinical trial, skin reactions at the site of application were reported with AndroGel, but none was severe enough to require treatment or discontinuation of drug.

Six patients (4%) in this trial had adverse events that led to discontinuation of AndroGel. These events included: cerebral hemorrhage, convulsion (neither of which were considered related to AndroGel administration), depression, sadness, memory loss, elevated prostate specific antigen, and hypertension. No AndroGel patient discontinued due to skin reactions.

In a separate uncontrolled pharmacokinetic study of 10 patients, two had adverse events associated with AndroGel; these were asthenia and depression in one patient and increased libido and hyperkinesia in the other.

In a 3 year, flexible dose, extension study, the incidence of all adverse events judged by the investigator to be at least possibly related to treatment with AndroGel and reported by > 1% of patients is shown in Table 3.

Table 3: Adverse Events Possibly, Probably or Definitely Related to Use of AndroGel in the 3 Year, Flexible Dose, Extension Study
Adverse Event | Percent of Subjects
 | (N = 162)
Lab Test Abnormal+ | 9.3
Skin dry | 1.9
Application Site Reaction | 5.6
Acne | 3.1
Pruritus | 1.9
Enlarged Prostate | 11.7
Carcinoma of Prostate | 1.2
Urinary Symptoms* | 3.7
Testis Disorder** | 1.9
Gynecomastia | 2.5
Anemia | 2.5
+Lab test abnormal occurred in 15 patients with one or more of the following events reported: elevated AST, elevated ALT, elevated testosterone, elevated hemoglobin or hematocrit, elevated cholesterol, elevated cholesterol/LDL ratio, elevated triglycerides, elevated HDL, elevated serum creatinine.
*Urinary symptoms included nocturia, urinary hesitancy, urinary incontinence, urinary retention, urinary urgency and weak urinary stream.
**Testis disorders included three patients. There were two with a non-palpable testis and one with slight right testicular tenderness.

Two patients reported serious adverse events considered possibly related to treatment: deep vein thrombosis (DVT) and prostate disorder requiring a transurethral resection of the prostate (TURP).

Discontinuation for adverse events in this study included: two patients with application site reactions, one with kidney failure, and five with prostate disorders (including increase in serum PSA in 4 patients, and increase in PSA with prostate enlargement in a fifth patient).

Increases in Serum PSA Observed in Clinical Trials of Hypogonadal Men

During the initial 6-month study, the mean change in PSA values had a statistically significant increase of 0.26 ng/mL. Serum PSA was measured every 6 months thereafter in the 162 hypogonadal men on AndroGel in the 3-year extension study. There was no additional statistically significant increase observed in mean PSA from 6 months through 36 months. However, there were increases in serum PSA observed in approximately 18% of individual patients. The overall mean change from baseline in serum PSA values for the entire group from month 6 to 36 was 0.11 ng/mL.

Twenty-nine patients (18%) met the per-protocol criterion for increase in serum PSA, defined as >2X the baseline or any single serum PSA >6 ng/mL. Most of these (25/29) met this criterion by at least doubling of their PSA from baseline. In most cases where PSA at least doubled (22/25), the maximum serum PSA value was still <2 ng/mL. The first occurrence of a pre-specified, post-baseline increase in serum PSA was seen at or prior to Month 12 in most of the patients who met this criterion (23 of 29; 79%).

Four patients met this criterion by having a serum PSA >6 ng/mL and in these, maximum serum PSA values were 6.2 ng/mL, 6.6 ng/mL, 6.7 ng/mL, and 10.7 ng/mL. In two of these patients, prostate cancer was detected on biopsy. The first patient's PSA levels were 4.7 ng/mL and 6.2 ng/mL at baseline and at Month 6/Final, respectively. The second patient's PSA levels were 4.2 ng/mL, 5.2 ng/mL, 5.8 ng/mL, and 6.6 ng/mL at baseline, Month 6, Month 12, and Final, respectively.

6.2 Postmarketing Experience

The following adverse reactions have been identified during post approval use of AndroGel. Because the reactions are reported voluntarily from a population of uncertain size, it is not always possible to reliably estimate their frequency or establish a causal relationship to drug exposure.

Secondary Exposure to Testosterone in Children

Cases of secondary exposure to testosterone resulting in virilization of children have been reported in postmarket surveillance. Signs and symptoms of these reported cases have included enlargement of the clitoris (with surgical intervention) or the penis, development of pubic hair, increased erections and libido, aggressive behavior, and advanced bone age. In most cases with a reported outcome, these signs and symptoms were reported to have regressed with removal of the testosterone gel exposure. In a few cases, however, enlarged genitalia did not fully return to age appropriate normal size, and bone age remained modestly greater than chronological age. In some of the cases, direct contact with the sites of application on the skin of men using testosterone gel was reported. In at least one reported case, the reporter considered the possibility of secondary exposure from items such as the testosterone gel user's shirts and/or other fabric, such as towels and sheets [see Warnings and Precautions (5.2)].

Hypogonadal Men

Table 4 includes adverse reactions that have been identified postmarketing.

Table 4: Adverse Drug Reactions from Postmarketing Experience of AndroGel by MedDRA System Organ Class
Blood and the lymphatic system disorders: | Elevated Hgb, Hct (polycythemia)
Endocrine disorders: | Hirsutism
Gastrointestinal disorders: | Nausea
General disorders and administration site reactions: | Asthenia, edema, malaise
Genitourinary disorders: | Impaired urination
Hepatobiliary disorders: | Abnormal liver function tests (e.g. transaminases, elevated GGTP, bilirubin)
Investigations: | Elevated PSA, electrolyte changes (nitrogen, calcium, potassium, phosphorus, sodium), changes in serum lipids (hyperlipidemia, elevated triglycerides, decreased HDL), impaired glucose tolerance, fluctuating testosterone levels, weight increase
Neoplasms benign, malignant and unspecified (cysts and polyps): | Prostate cancer
Nervous system: | Headache, dizziness, sleep apnea, insomnia
Psychiatric disorders: | Depression, emotional lability, decreased libido, nervousness, hostility, amnesia, anxiety
Reproductive system and breast disorders: | Gynecomastia, mastodynia, prostatic enlargement, testicular atrophy, oligospermia, priapism (frequent or prolonged erections)
Respiratory disorders: | Dyspnea
Skin and subcutaneous tissue disorders: | Acne, alopecia, application site reaction (pruritus, dry skin, erythema, rash, discolored hair, paresthesia), sweating
Vascular disorders: | Hypertension, vasodilation (hot flushes)

7 DRUG INTERACTIONS

7.1 Insulin

Changes in insulin sensitivity or glycemic control may occur in patients treated with androgens. In diabetic patients, the metabolic effects of androgens may decrease blood glucose and, therefore, insulin requirements.

7.2 Corticosteroids

The concurrent use of testosterone with ACTH or corticosteroids may result in increased fluid retention and should be monitored cautiously, particularly in patients with cardiac, renal or hepatic disease.

7.3 Oral Anticoagulants

Changes in anticoagulant activity may be seen with androgens. More frequent monitoring of INR and prothrombin time are recommended in patients taking anticoagulants, especially at the initiation and termination of androgen therapy.

8 USE IN SPECIFIC POPULATIONS

8.1 Pregnancy

Pregnancy Category X: AndroGel is contraindicated during pregnancy or in women who may become pregnant. It is teratogenic and may cause fetal harm [see Contraindications (4)]. Exposure of a female fetus to androgens may result in varying degrees of virilization. If this drug is used during pregnancy, or if the patient becomes pregnant while taking this drug, the patient should be apprised of the potential hazard to a fetus.

8.3 Nursing Mothers

Although it is not known how much testosterone transfers into human milk, AndroGel is contraindicated in nursing women because of the potential for serious adverse reactions in nursing infants [see Contraindications (4)].

Testosterone and other androgens may adversely affect lactation.

8.4 Pediatric Use

Safety and efficacy of AndroGel in males < 18 years old has not been established. Improper use may result in acceleration of bone age and premature closure of epiphyses.

8.5 Geriatric Use

There have not been sufficient numbers of geriatric patients involved in controlled clinical studies utilizing AndroGel to determine whether efficacy in those over 65 years of age differs from younger subjects. Additionally, there is insufficient long-term safety data in geriatric patients to assess the potential risks of cardiovascular disease and prostate cancer.

8.6 Renal or Hepatic Impairment

No formal studies were conducted involving patients with renal or hepatic insufficiencies.

9 DRUG ABUSE AND DEPENDENCE

9.1 Controlled Substance

AndroGel contains testosterone, a Schedule III controlled substance as defined by the Anabolic Steroids Control Act.

Oral ingestion of AndroGel will not result in clinically significant serum testosterone concentrations due to extensive first-pass metabolism.

10 OVERDOSAGE

There is one report of acute overdosage with use of an approved injectable testosterone product: this subject had serum testosterone levels of up to 11,400 ng/dL with a cerebrovascular accident. Treatment of overdosage would consist of discontinuation of AndroGel together with appropriate symptomatic and supportive care.

11 DESCRIPTION

AndroGel (testosterone gel) 1% is a clear, colorless hydroalcoholic gel containing 1% testosterone. Topical administration of AndroGel 5 g, 7.5 g, or 10 g contains 50 mg, 75 mg, or 100 mg of testosterone, respectively, is to be applied daily to the skin's surface. Approximately 10% of the applied testosterone dose is absorbed across skin of average permeability during a 24-hour period.

The active pharmacologic ingredient in AndroGel is testosterone. Testosterone USP is a white to practically white crystalline powder chemically described as 17-beta hydroxyandrost-4-en-3-one. The structural formula is:

Inactive ingredients in AndroGel are carbomer 980, ethanol 67.0%, isopropyl myristate, purified water, and sodium hydroxide. These ingredients are not pharmacologically active.

12 CLINICAL PHARMACOLOGY

12.1 Mechanism of Action

Endogenous androgens, including testosterone and dihydrotestosterone (DHT), are responsible for the normal growth and development of the male sex organs and for maintenance of secondary sex characteristics. These effects include the growth and maturation of prostate, seminal vesicles, penis and scrotum; the development of male hair distribution, such as facial, pubic, chest and axillary hair; laryngeal enlargement, vocal chord thickening, alterations in body musculature and fat distribution. Testosterone and DHT are necessary for the normal development of secondary sex characteristics. Male hypogonadism results from insufficient secretion of testosterone and is characterized by low serum testosterone concentrations. Signs/symptoms associated with male hypogonadism include erectile dysfunction and decreased sexual desire, fatigue and loss of energy, mood depression, regression of secondary sexual characteristics and osteoporosis.

Male hypogonadism has two main etiologies. Primary hypogonadism is caused by defects of the gonads, such as Klinefelter's Syndrome or Leydig cell aplasia, whereas secondary hypogonadism is the failure of the hypothalamus (or pituitary) to produce sufficient gonadotropins (FSH, LH).

12.3 Pharmacokinetics

Adult Males

Absorption

AndroGel delivers physiologic amounts of testosterone, producing circulating testosterone concentrations that approximate normal levels (298 – 1043 ng/dL) seen in healthy men. AndroGel provides continuous transdermal delivery of testosterone for 24 hours following a single application to intact, clean, dry skin of the shoulders, upper arms and/or abdomen.

AndroGel is a hydroalcoholic formulation that dries quickly when applied to the skin surface. The skin serves as a reservoir for the sustained release of testosterone into the systemic circulation. Approximately 10% of the testosterone dose applied on the skin surface from AndroGel is absorbed into systemic circulation. Therefore, 5 g and 10 g of AndroGel systemically deliver approximately 5 mg and 10 mg of testosterone, respectively. In a study with 10 g of AndroGel, all patients showed an increase in serum testosterone within 30 minutes, and eight of nine patients had a serum testosterone concentration within normal range by 4 hours after the initial application. Absorption of testosterone into the blood continues for the entire 24-hour dosing interval. Serum concentrations approximate the steady-state level by the end of the first 24 hours and are at steady state by the second or third day of dosing.

With single daily applications of AndroGel, follow-up measurements 30, 90 and 180 days after starting treatment have confirmed that serum testosterone concentrations are generally maintained within the eugonadal range. Figure 1 summarizes the 24-hour pharmacokinetic profiles of testosterone for hypogonadal men (<300 ng/dL) maintained on 5 g or 10 g of AndroGel for 30 days. The average (± SD) daily testosterone concentration produced by AndroGel 10 g on Day 30 was 792 (± 294) ng/dL and by AndroGel 5 g 566 (± 262) ng/dL.

Figure 1: Mean (± SD) Steady-State Serum Testosterone Concentrations on Day 30 in Patients Applying AndroGel Once Daily

When AndroGel treatment is discontinued after achieving steady state, serum testosterone levels remain in the normal range for 24 to 48 hours but return to their pretreatment levels by the fifth day after the last application.

Distribution

Circulating testosterone is primarily bound in the serum to sex hormone-binding globulin (SHBG) and albumin. Approximately 40% of testosterone in plasma is bound to SHBG, 2% remains unbound (free) and the rest is bound to albumin and other proteins.

Metabolism

There is considerable variation in the half-life of testosterone as reported in the literature, ranging from 10 to 100 minutes. Testosterone is metabolized to various 17-keto steroids through two different pathways. The major active metabolites of testosterone are estradiol and DHT.

DHT concentrations increased in parallel with testosterone concentrations during AndroGel treatment. After 180 days of treatment in adult males, mean DHT concentrations were within the normal range with 5 g AndroGel and were about 7% above the normal range after a 10 g dose. The mean steady-state DHT/T ratio during 180 days of AndroGel treatment remained within normal limits and ranged from 0.23 to 0.29 (5 g/day) and from 0.27 to 0.33 (10 g/day).

Excretion

About 90% of a dose of testosterone given intramuscularly is excreted in the urine as glucuronic and sulfuric acid conjugates of testosterone and its metabolites; about 6% of a dose is excreted in the feces, mostly in the unconjugated form. Inactivation of testosterone occurs primarily in the liver.

13 NONCLINICAL TOXICOLOGY

13.1 Carcinogenesis, Mutagenesis, Impairment of Fertility

Testosterone has been tested by subcutaneous injection and implantation in mice and rats. In mice, the implant induced cervical-uterine tumors, which metastasized in some cases. There is suggestive evidence that injection of testosterone into some strains of female mice increases their susceptibility to hepatoma. Testosterone is also known to increase the number of tumors and decrease the degree of differentiation of chemically induced carcinomas of the liver in rats.

14 CLINICAL STUDIES

14.1 Clinical Trials in Adult Hypogonadal Males

AndroGel was evaluated in a multi-center, randomized, parallel-group, active-controlled, 180-day trial in 227 hypogonadal men. The study was conducted in 2 phases. During the Initial Treatment Period (Days 1-90), 73 patients were randomized to AndroGel 5 g daily, 78 patients to AndroGel 10 g daily, and 76 patients to a non-scrotal testosterone transdermal system. The study was double-blind for dose of AndroGel but open-label for active control. Patients who were originally randomized to AndroGel and who had single-sample serum testosterone levels above or below the normal range on Day 60 were titrated to 7.5 g daily on Day 91. During the Extended Treatment Period (Days 91-180), 51 patients continued on AndroGel 5 g daily, 52 patients continued on AndroGel 10 g daily, 41 patients continued on a non-scrotal testosterone transdermal system (5 mg daily), and 40 patients received AndroGel 7.5 g daily. Upon completion of the initial study, 163 enrolled and 162 patients received treatment in an open-label extension study of AndroGel for an additional period of up to 3 years.

Mean peak, trough and average serum testosterone concentrations within the normal range (298-1043 ng/dL) were achieved on the first day of treatment with doses of 5 g and 10 g. In patients continuing on AndroGel 5 g and 10 g, these mean testosterone levels were maintained within the normal range for the 180-day duration of the original study. Figure 2 summarizes the 24-hour pharmacokinetic profiles of testosterone administered as AndroGel for 30, 90 and 180 days. Testosterone concentrations were maintained as long as the patient continued to properly apply the prescribed AndroGel treatment.

Figure 2: Mean Steady-State Testosterone Concentrations in Patients with Once-Daily AndroGel Therapy

Table 5 summarizes the mean testosterone concentrations on Treatment Day 180 for patients receiving 5 g, 7.5 g, or 10 g of AndroGel. The 7.5 g dose produced mean concentrations intermediate to those produced by 5 g and 10 g of AndroGel.

Table 5: Mean (± SD) Steady-State Serum Testosterone Concentrations During Therapy (Day 180)
 | 5 g | 7.5 g | 10 g
 | N = 44 | N = 37 | N = 48
Cavg | 555 ± 225 | 601 ± 309 | 713 ± 209
Cmax | 830 ± 347 | 901 ± 471 | 1083 ± 434
Cmin | 371 ± 165 | 406 ± 220 | 485 ± 156

Of 129 hypogonadal men who were appropriately titrated with AndroGel and who had sufficient data for analysis, 87% achieved an average serum testosterone level within the normal range on Treatment Day 180.

In patients treated with AndroGel, there were no observed differences in the average daily serum testosterone concentrations at steady-state based on age, cause of hypogonadism, or body mass index.

AndroGel 5 g/day and 10 g/day resulted in significant increases over time in total body mass and total body lean mass, while total body fat mass and the percent body fat decreased significantly. These changes were maintained for 180 days of treatment during the original study. Changes in the 7.5 g dose group were similar. Bone mineral density in both hip and spine increased significantly from Baseline to Day 180 with 10 g AndroGel.

AndroGel treatment at 5 g/day and 10 g/day for 90 days produced significant improvement in libido (measured by sexual motivation, sexual activity and enjoyment of sexual activity as assessed by patient responses to a questionnaire). The degree of penile erection as subjectively estimated by the patients, increased with AndroGel treatment, as did the subjective score for “satisfactory duration of erection.” AndroGel treatment at 5 g/day and 10 g/day produced positive effects on mood and fatigue. Similar changes were seen after 180 days of treatment and in the group treated with the 7.5 g dose. DHT concentrations increased in parallel with testosterone concentrations at AndroGel doses of 5 g/day and 10 g/day, but the DHT/T ratio stayed within the normal range, indicating enhanced availability of the major physiologically active androgen. Serum estradiol (E2) concentrations increased significantly within 30 days of starting treatment with AndroGel 5 or 10 g/day and remained elevated throughout the treatment period but remained within the normal range for eugonadal men. Serum levels of SHBG decreased very slightly (1 to 11%) during AndroGel treatment. In men with hypergonadotropic hypogonadism, serum levels of LH and FSH fell in a dose- and time-dependent manner during treatment with AndroGel.

14.2 Phototoxicity in Humans

The phototoxic potential of AndroGel was evaluated in a double-blind, single-dose study in 27 subjects with photosensitive skin types. The Minimal Erythema Dose (MED) of ultraviolet radiation was determined for each subject. A single 24 (+1) hour application of duplicate patches containing test articles (placebo gel, testosterone gel, or saline) was made to naive skin sites on Day 1. On Day 2, each subject received five exposure times of ultraviolet radiation, each exposure being 25% greater than the previous one. Skin evaluations were made on Days 2 to 5. Exposure of test and control article application sites to ultraviolet light did not produce increased inflammation relative to non-irradiated sites, indicating no phototoxic effect.

14.3 Testosterone Transfer from Male Patients to Female Partners

The potential for dermal testosterone transfer following AndroGel use was evaluated in a clinical study between males dosed with AndroGel and their untreated female partners. Two (2) to 12 hours after AndroGel (10 g) application by the male subjects, the couples (N = 38 couples) engaged in daily, 15-minute sessions of vigorous skin-to-skin contact so that the female partners gained maximum exposure to the AndroGel application sites. Under these study conditions, all unprotected female partners had a serum testosterone concentration >2 times the baseline value at some time during the study. When a shirt covered the application site(s), the transfer of testosterone from the males to the female partners was completely prevented.

16 HOW SUPPLIED/STORAGE AND HANDLING

AndroGel is supplied in non-aerosol, metered-dose pumps. The pump is composed of plastic and stainless steel and an LDPE/aluminum foil inner liner encased in rigid plastic with a polypropylene cap. Each 88 g AndroGel Pump in the twin package is capable of dispensing 75 g or 60 metered 1.25 g doses.

AndroGel is also supplied in unit-dose aluminum foil packets in cartons of 30. Each packet of 2.5 g or 5 g gel contains 25 mg or 50 mg testosterone, respectively.

NDC Number | Package Size
54868-5814-0 | 2 x 75 g pumps (each pump dispenses 60 metered 1.25 g doses)
54868-4792-0 | 30 packets (2.5 g per packet)
54868-4810-0 | 30 packets (5 g per packet)

Keep AndroGel out of the reach of children.

Storage

Store at 25°C (77°F); excursions permitted to 15° to 30°C (59° to 86°F) [see USP Controlled Room Temperature].

Disposal

Used AndroGel pumps or used AndroGel packets should be discarded in household trash in a manner that prevents accidental application or ingestion by children or pets.

17 PATIENT COUNSELING INFORMATION

See FDA-Approved Medication Guide

17.2 Potential for Secondary Exposure to Testosterone and Steps to Prevent Secondary Exposure

Secondary exposure to testosterone in children and women can occur with the use of testosterone gel in men. Cases of secondary exposure to testosterone have been reported in children with signs and symptoms including enlargement of the penis or clitoris, premature development of pubic hair, increased erections, and aggressive behavior.

- Physicians should advise patients of the reported signs and symptoms of secondary exposure which may include the following:
  - In children; unexpected sexual development including inappropriate enlargement of the penis or clitoris, premature development of pubic hair, increased erections, and aggressive behavior
  - In women; changes in hair distribution, increase in acne, or other signs of testosterone effects
- The possibility of secondary exposure to testosterone gel should be brought to the attention of a healthcare provider
- Testosterone gel should be promptly discontinued until the cause of virilization is identified

Strict adherence to the following precautions is advised to minimize the potential for secondary exposure to testosterone from testosterone gel in men [see FDA-Approved Medication Guide]:

- Children and women should avoid contact with unwashed or unclothed application site(s) of men using testosterone gel
- To minimize the potential for transfer to others, patients using AndroGel should apply the product as directed and strictly adhere to the following:
  - Wash hands with soap and water after application
  - Cover the application site(s) with clothing after the gel has dried
  - Wash the application site(s) thoroughly with soap and water prior to any situation where skin-to-skin contact of the application site with another person is anticipated
  - In the event that unwashed or unclothed skin to which testosterone gel has been applied comes in contact with the skin of another person, the general area of contact on the other person should be washed with soap and water as soon as possible.

17.3 Potential Adverse Reactions with Androgens

Patients should be informed that treatment with androgens may lead to adverse reactions which include:

- Changes in urinary habits such as increased urination at night, trouble starting your urine stream, passing urine many times during the day, having an urge that you have to go to the bathroom right away, having a urine accident, being unable to pass urine and weak urine flow.
- Breathing disturbances, including those associated with sleep, or excessive daytime sleepiness.
- Too frequent or persistent erections of the penis.
- Nausea, vomiting, changes in skin color, or ankle swelling.

17.4 Patients Should Be Advised

- To read the Medication Guide before starting AndroGel therapy and to reread it each time the prescription is renewed
- Of the appropriate application and use of AndroGel to maximize the benefits and to minimize the risk of secondary exposure in children and women
- To keep AndroGel out of the reach of children
- That AndroGel is an alcohol based product and is flammable; therefore avoid fire, flame or smoking until the gel has dried
- Of the importance of adhering to all recommended monitoring
- To report any changes in their state of health, such as changes in urinary habits, breathing, sleep, and mood
- To wait 5 hours before showering or swimming. This will ensure that the greatest amount of AndroGel is absorbed into their system.

Marketed By:
Abbott Laboratories
North Chicago, IL 60064, U.S.A.

U.S. Patent No. 6,503,894

© 2011 Abbott Laboratories

53267/53268 5E Rev Nov 2011

Additional barcode label applied by:
Physicians Total Care, Inc.
Tulsa, Oklahoma 74146

Medication Guide

AndroGel® (AN DROW JEL) CIII

(testosterone gel) 1%

Read the Medication Guide that comes with AndroGel before you start taking it and each time you get a refill. There may be new information. This Medication Guide does not take the place of talking to your healthcare provider about your medical condition or your treatment.

What is the most important information I should know about AndroGel?

1. Early signs and symptoms of puberty have happened in young children who were accidentally exposed to testosterone through contact with men using AndroGel.

Signs and symptoms of early puberty in a child may include:

- enlarged penis or clitoris
- early development of pubic hair
- increased erections or sex drive
- aggressive behavior

AndroGel can transfer from your body to others.

2. Women and children should avoid contact with the unwashed or unclothed area where AndroGel has been applied to your skin.

Stop using AndroGel and call your healthcare provider right away if you see any signs and symptoms in a child or a woman that may have occurred through accidental exposure to AndroGel.

Signs and symptoms of exposure to AndroGel in children may include:

- enlarged penis or clitoris
- early development of pubic hair
- increased erections or sex drive
- aggressive behavior

Signs and symptoms of exposure to AndroGel in women may include:

- changes in body hair
- a large increase in acne

To lower the risk of transfer of AndroGel from your body to others, you should follow these important instructions:

- Apply AndroGel only to areas that will be covered by a short sleeve T-shirt. These areas are your shoulders and upper arms, or stomach area (abdomen), or shoulders, upper arms and stomach area.
- Wash your hands right away with soap and water after applying AndroGel.
- After the gel has dried, cover the application area with clothing. Keep the area covered until you have washed the application area well or have showered.
- If you expect to have skin-to-skin contact with another person, first wash the application area well with soap and water.
- If a woman or child makes contact with the AndroGel application area, that area on the woman or child should be washed well with soap and water right away.

What is AndroGel?

AndroGel is a prescription medicine that contains testosterone. AndroGel is used to treat adult males who have low or no testosterone.

It is not known if AndroGel is safe or effective in children younger than 18 years old. Improper use of AndroGel may affect bone growth in children.

AndroGel is a controlled substance (CIII) because it contains testosterone that can be a target for people who abuse prescription medicines. Keep your AndroGel in a safe place to protect it. Never give your AndroGel to anyone else, even if they have the same symptoms you have. Selling or giving away this medicine may harm others and is against the law.

AndroGel is not meant for use in women.

Who should not use AndroGel?

Do not use AndroGel if you:

- have breast cancer
- have or might have prostate cancer
- are pregnant or may become pregnant or breast-feeding. AndroGel may harm your unborn or breast-feeding baby.

Women who are pregnant or who may become pregnant should avoid contact with the area of skin where AndroGel has been applied.

- are allergic to testosterone or any of the ingredients in AndroGel including soy. See the end of this Medication Guide for a complete list of ingredients in AndroGel.

Talk to your healthcare provider before taking this medicine if you have any of the above conditions.

What should I tell my healthcare provider before using AndroGel?

Before you use AndroGel, tell your healthcare provider if you:

- have breast cancer or prostate cancer
- have urinary problems due to an enlarged prostate
- have heart problems
- have liver or kidney problems
- have problems breathing while you sleep (sleep apnea)
- have any other medical conditions

Tell your healthcare provider about all the medicines you take, including prescription and non-prescription medicines, vitamins, and herbal supplements.

Using AndroGel with certain other medicines can affect each other.

Especially, tell your healthcare provider if you take:

- insulin
- corticosteroids
- medicines that decrease blood clotting

Ask your healthcare provider or pharmacist for a list of these medicines, if you are not sure.

Know the medicines you take. Keep a list of them and show it to your healthcare provider and pharmacist when you get a new medicine.

How should I use AndroGel?

- It is important that you apply AndroGel exactly as prescribed by your healthcare provider. Your healthcare provider will tell you how much AndroGel to apply and when to apply it.
- Your healthcare provider may change your AndroGel dose. Do not change your AndroGel dose without talking to your healthcare provider.
- AndroGel is for skin use only.
- Do not allow others to apply AndroGel to your body.
- Applying AndroGel:

AndroGel comes in a pump or in packets.
  If you are using the AndroGel pump:
    - Before using the pump for the first time, you will need to prime the pump. To prime AndroGel, fully push down on the pump 3 times. Do not use any AndroGel that came out while priming. Wash it down the sink or throw it in the trash to avoid accidental exposure to others. Your AndroGel pump is ready to use now.
    - Your healthcare provider will tell you the number of times to press the pump for each dose.
  If you are using AndroGel packets:
    - Tear open the packet completely at the dotted line.
    - Squeeze all of the AndroGel out of the packet into the palm of your hand. Squeeze from the bottom of the packet to the top.
    - Throw away the packet in the trash out of the reach of children to avoid accidental exposure.

- Squeeze the medicine into the palm of your hand and apply to clean dry, intact skin at the same time each day.
- You may also apply AndroGel from the pump or packet directly to your skin.
- Apply AndroGel only to areas that will be covered by a short sleeve t-shirt, as shown in the shaded areas in the figure below. These areas are your shoulders and upper arms, or stomach area, or shoulders, upper arm and stomach area.
- Do not apply AndroGel to your penis or scrotum.
- Wash your hands with soap and water right after you apply AndroGel.
- Let the application areas dry for a few minutes before putting on a shirt.
- To prevent transfer of AndroGel to others, clothes (such as a t-shirt) should always be worn to cover the AndroGel application areas until you have washed the application areas well with soap and water.

- Wait 5 hours before showering or swimming. This will ensure that the greatest amount of AndroGel is absorbed into your system.
- AndroGel is flammable until dry. Let the gel dry before smoking or going near an open flame.

Your healthcare provider will test your blood before you start and while you take AndroGel.

What are the possible side effects of AndroGel?

AndroGel can cause serious side effects including:

See “What is the most important information I should know about AndroGel?”

- If you already have enlargement of your prostate gland your signs and symptoms can get worse while using AndroGel. This can include:

- increased urination at night
- trouble starting your urine stream
- having to pass urine many times during the day
- having an urge that you have to go to the bathroom right away
- having a urine accident
- being unable to pass urine or weak urine flow

- Possible increased risk of prostate cancer. Your healthcare provider should check you for prostate cancer or any other prostate problems before you start and while you use AndroGel.
- In large doses AndroGel may lower your sperm count.
- Swelling of your ankles, feet, or body, with or without heart failure.
- Enlarged or painful breasts.
- Have problems breathing while you sleep (sleep apnea).
- Blood clots in the legs. This can include pain, swelling or redness of your legs.

Call your healthcare provider right away if you have any of the serious side effects listed above.

The most common side effects of AndroGel include:

- acne
- skin irritation where AndroGel is applied
- increased cholesterol levels
- increased prostate specific antigen (a test used to screen for prostate cancer)
- increased red blood cell count
- increased liver function tests

Other side effects include more erections than are normal for you or erections that last a long time.

Tell your healthcare provider if you have any side effect that bothers you or that does not go away.

These are not all the possible side effects of AndroGel. For more information, ask your healthcare provider or pharmacist.

Call your doctor for medical advice about side effects. You may report side effects to FDA at 1-800-FDA-1088.

How should I store AndroGel?

- Store AndroGel between 59ºF to 86ºF (15ºC to 30ºC).
- Safely throw away used AndroGel in household trash. Be careful to prevent accidental exposure of children or pets.
- Keep AndroGel away from fire.

Keep AndroGel and all medicines out of the reach of children.

General information about AndroGel

Medicines are sometimes prescribed for purposes other than those listed in a Medication Guide. Do not use AndroGel for a condition for which it was not prescribed. Do not give AndroGel to other people, even if they have the same symptoms you have. It may harm them.

This Medication Guide summarizes the most important information about AndroGel. If you would like more information, talk to your healthcare provider. You can ask your pharmacist or healthcare provider for information about AndroGel that is written for health professionals.

For more information, go to www.ANDROGEL.com or call 1-800-241-1643.

What are the ingredients in AndroGel?
Active ingredient: testosterone
Inactive ingredients: carbomer 980, ethyl alcohol 67.0%, isopropyl myristate, purified water and sodium hydroxide.

© 2011 Abbott Laboratories

Marketed by:

Abbott Laboratories

North Chicago, IL 60064, U.S.A.

This Medication Guide has been approved by the U.S. Food and Drug Administration.

Issued Nov 2011

PACKAGE LABEL

NDC 54868-4792-0

CIII

AndroGel® (testosterone gel) 1%

30 Unit-dose Packets

Contains 2.5 grams per unit dose

Clear, colorless gel provides transdermal delivery of testosterone through the skin of the shoulders, upper arms, or abdomen.*

Rx Only

Dispense the enclosed Medication Guide to each patient.

* See accompanying package insert.

PACKAGE LABEL

NDC 54868-4810-0

CIII

AndroGel® (testosterone gel 1%)

30 Unit-dose Packets

Contains 5 grams per unit dose

Clear, colorless gel provides transdermal delivery of testosterone through the skin of the shoulders, upper arms, or abdomen.*

Dispense the enclosed Medication guide to each patient.

*See accompanying package insert.

Rx Only

PACKAGE LABEL

NDC 54868-5814-0

CIII

AndroGel® (testosterone 1% Pump

This package contains 2 multi-dose pumps. Each pump is capable of dispensing 75g doses each.

Clear, colorless gel provides transdermal delivery of testosterone through the skin of the shoulders, upper arms, or abdomen.*

Dispense the enclosed Medication Guide to each patient.

Rx Only